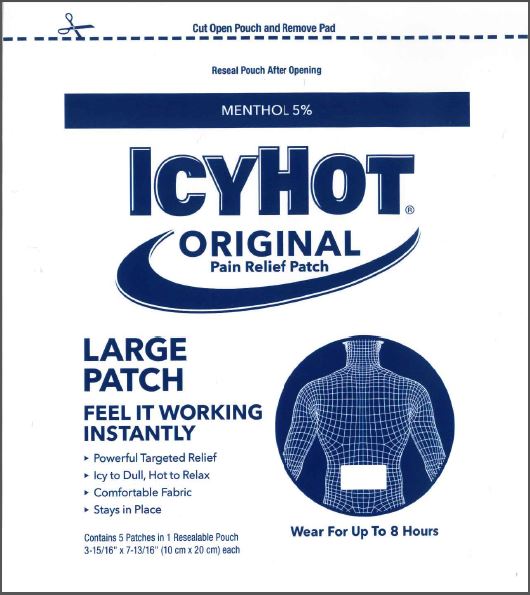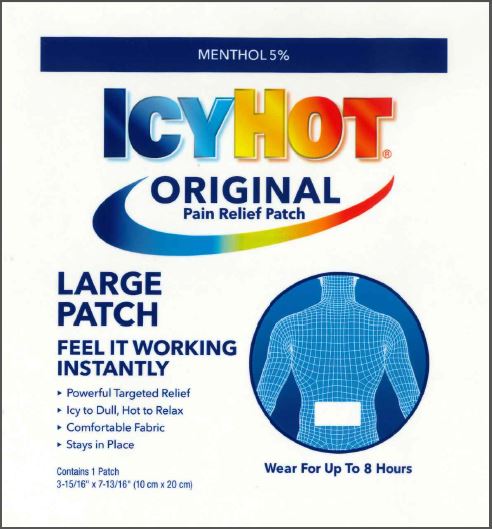 DRUG LABEL: Icy Hot
NDC: 62168-0853 | Form: PATCH
Manufacturer: Lead Chemical Co., Ltd.
Category: otc | Type: HUMAN OTC DRUG LABEL
Date: 20250422

ACTIVE INGREDIENTS: MENTHOL, UNSPECIFIED FORM 428.5 mg/1 1
INACTIVE INGREDIENTS: ALUMINUM HYDROXIDE; CARBOXYMETHYLCELLULOSE SODIUM, UNSPECIFIED; GLYCERIN; ISOPROPYL MYRISTATE; NONOXYNOL-30; POLYACRYLIC ACID (250000 MW); POLYSORBATE 80; SODIUM POLYACRYLATE (2500000 MW); SORBITAN SESQUIOLEATE; TALC; TARTARIC ACID; TITANIUM DIOXIDE; WATER

Icy Hot® Medicated Back Patch

Active Ingredient

Menthol 5%

Purpose

Topical analgesic

Uses

temporarily relieves minor pain associated with:

- arthritis
- simple backache
- bursitis
- tendonitis
- muscle strains
- sprains
- bruises
- cramps

Warnings

For external use only

When using this product

- use only as directed. Read and follow all directions and warnings on this label.
- avoid contact with eyes and mucous membranes
- rare cases of serious burns have been reported with products of this type
- do not apply to wounds or damaged, broken or irritated skin
- do not bandage tightly or apply local heat (such as heating pads) to the area of use
- a transient burning sensation may occur upon application but generally disappears in several days

Stop use and ask a doctor if

- condition worsens
- redness is present
- irritation develops
- symptoms persist for more than 7 days or clear up and occur again within a few days
- you experience signs of skin injury, such as pain, swelling, or blistering where the product was applied

If pregnant or breast-feeding,

ask a health professional before use.

Keep out of reach of children.

If swallowed, get medical help or contact a Poison Control Center right away.

Directions

adults and children over 12 years:

- remove backing from patch by firmly grasping both ends and gently pulling until backing separates in middle
- carefully remove smaller portion of backing from patch and apply exposed portion of patch to affected area
- once exposed portion of patch is positioned, carefully remove remaining backing to completely apply patch to affected area
- wear one Icy Hot patch for up to 8 hours
- repeat as necessary, but no more than 3 times daily

children 12 years or younger: ask a doctor

Inactive ingredients

aluminum hydroxide, cellulose gum, glycerin, isopropyl myristate, methyl acrylate/2-ethylhexyl acrylate copolymer, nonoxynol-30, polyacrylic acid, polysorbate 80, sodium polyacrylate, sorbitan sesquioleate, starch/acrylic acid graft copolymer sodium salt, talc, tartaric acid, titanium dioxide, water

Principal Display Panel – Large Patch (5 Patch Pouch)

MENTHOL 5%

ICY HOT®
ORIGINAL
Pain Relief Patch

LARGE
PATCH

FEEL IT WORKING
INSTANTLY

- Powerful Targeted Relief
- Icy to Dull, Hot to Relax
- Comfortable Fabric
- Stays in Place

Wear For Up To 8 Hours

Contains 5 Patches in 1 Resealable Pouch
3-15/16” x 7-13/16” (10 cm x 20 cm) each

CHATTEM®
A SANOFI COMPANY
Dist. by Chattem, Inc., a Sanofi Company
P.O. Box 2219
Chattanooga, TN 37409-0219 USA
©2020 www.icyhot.com
Made in Japan

Pouch Label

Principal Display Panel – Large Patch (Single Patch Pouch)

MENTHOL 5%

ICY HOT®
ORIGINAL
Pain Relief Patch

LARGE
PATCH

FEEL IT WORKING
INSTANTLY

- Powerful Targeted Relief
- Icy to Dull, Hot to Relax
- Comfortable Fabric
- Stays in Place

Wear For Up To 8 Hours

Contains 1 Patch
3-15/16” x 7-13/16” (10 cm x 20 cm)

CHATTEM®
A SANOFI COMPANY
Dist. by Chattem, Inc., a Sanofi Company
P.O. Box 2219
Chattanooga, TN 37409-0219 USA
©2020 www.icyhot.com
Made in Japan

Pouch Label